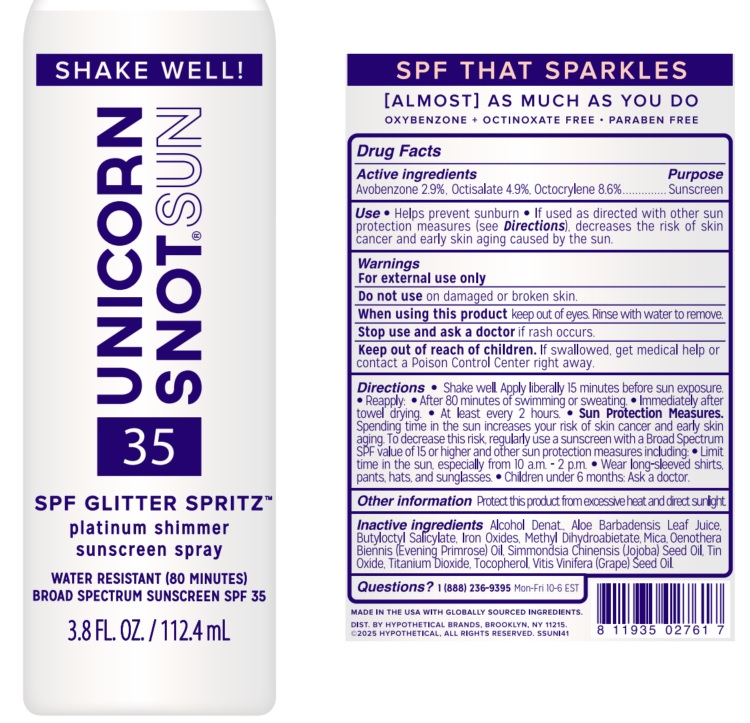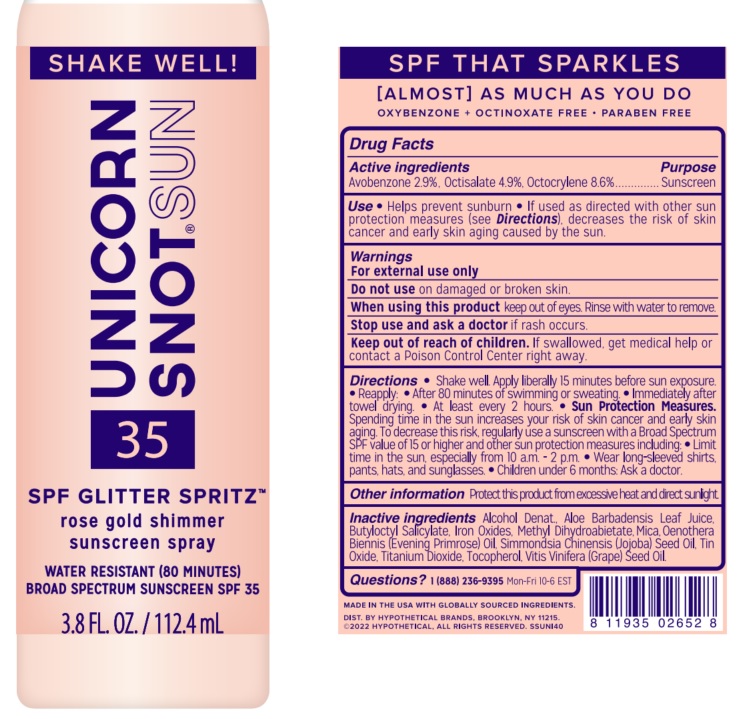 DRUG LABEL: Unicorn Snot 35 SPF Glitter Spritz
NDC: 72192-024 | Form: SPRAY
Manufacturer: Jailbreak Toys, Inc. DBA UNICORN SNOT
Category: otc | Type: HUMAN OTC DRUG LABEL
Date: 20260101

ACTIVE INGREDIENTS: OCTOCRYLENE 8.6 g/100 mL; AVOBENZONE 2.9 g/100 mL; OCTISALATE 4.9 g/100 mL
INACTIVE INGREDIENTS: ALCOHOL; SIMMONDSIA CHINENSIS (JOJOBA) SEED OIL; TOCOPHEROL; METHYL DIHYDROABIETATE; TIN OXIDE; OENOTHERA BIENNIS (EVENING PRIMROSE) OIL; VITIS VINIFERA (GRAPE) SEED OIL; MICA; TITANIUM DIOXIDE; ALOE BARBADENSIS LEAF JUICE; FERROUS OXIDE; BUTYLOCTYL SALICYLATE

Unicorn Snot 35 SPF Glitter Spritz - Rose Gold Shimmer / Platinum Shimmer

Active ingredients

Avobenzone 2.9%, Octisalate 4.9%, Octocrylene 8.6%

Purpose

Sunscreen

INDICATIONS AND USAGE

Use • Helps prevent sunburn • If used as directed with other sun protection measures (see Directions), decreases the risk of skin cancer and early skin aging caused by the sun.

Warnings

For external use only

Do not use on damaged or broken skin.

When using this product keep out of eyes. Rinse with water to remove.

Stop use and ask a doctor if rash occurs.

Keep out of reach of children. If swallowed, get medical help or contact a Poison Control Center right away.

DOSAGE AND ADMINISTRATION

Directions • Shake well. Apply liberally 15 minutes before sun exposure. • Reapply: • After 80 minutes of swimming or sweating. • Immediately after towel drying. • At least every 2 hours. • Sun Protection Measures. Spending time in the sun increases your risk of skin cancer and early skin aging. To decrease this risk, regularly use a sunscreen with a Broad Spectrum SPF value of 15 or higher and other sun protection measures including: • Limit time in the sun, especially from 10 a.m. - 1 p.m. • Wear long-sleeved shirts, pants, hats, and sunglasses. • Children under 6 months: Ask a doctor.

Other information

Protect this product from excessive heat and direct sunlight.

INACTIVE INGREDIENT

Inactive ingredients Alcohol. Denat., Aloe Barbadensis Leaf Juice, Butyloctyl Salicylate, Iron Oxides, Methyl Dihydroabietate, Mica Oenothera Biennis (Evening Primrose) Oil, Simmondsia Chinesis (Jojoba) Seed Oil, Tin Oxide, Titanium Dioxide, Tocopherol, Vitis Vinifera (Grape) Seed Oil.

QUESTIONS

Questions?1(888) 236-9395 Mon-Fri 10-6 EST

SPF THAT SPARKLES

[ALMOST] AS MUCH AS YOU DO

OXYBENZONE + OCTINOXATE FREE • PARABEN FREE

MADE IN THE USA WITH GLOBALLY SOURCED INGREDIENTS.

DIST. BY HYPOTHETICAL BRANDS, BROOKLYN, NY 11215.

©2022 HYPOTHETICAL, ALL RIGHTS RESERVED. SSUN140

024 rose gold label

UNICORN SNOT®SUN 35

SPF GLITTER SPRITZ™

rose gold shimmer

sunscreen spray

WATER RESISTANT (80 MINUTES)

BROAD SPECTRUM SUNSCREEN SPF 35

3.8 FL. OZ. / 112.4 mL

025 platinum label

UNICORN SNOT®SUN 35

SPF GLITTER SPRITZ™

platinum shimmer

sunscreen spray

WATER RESISTANT (80 MINUTES)

BROAD SPECTRUM SUNSCREEN SPF 35

3.8 FL. OZ. / 112.4 mL